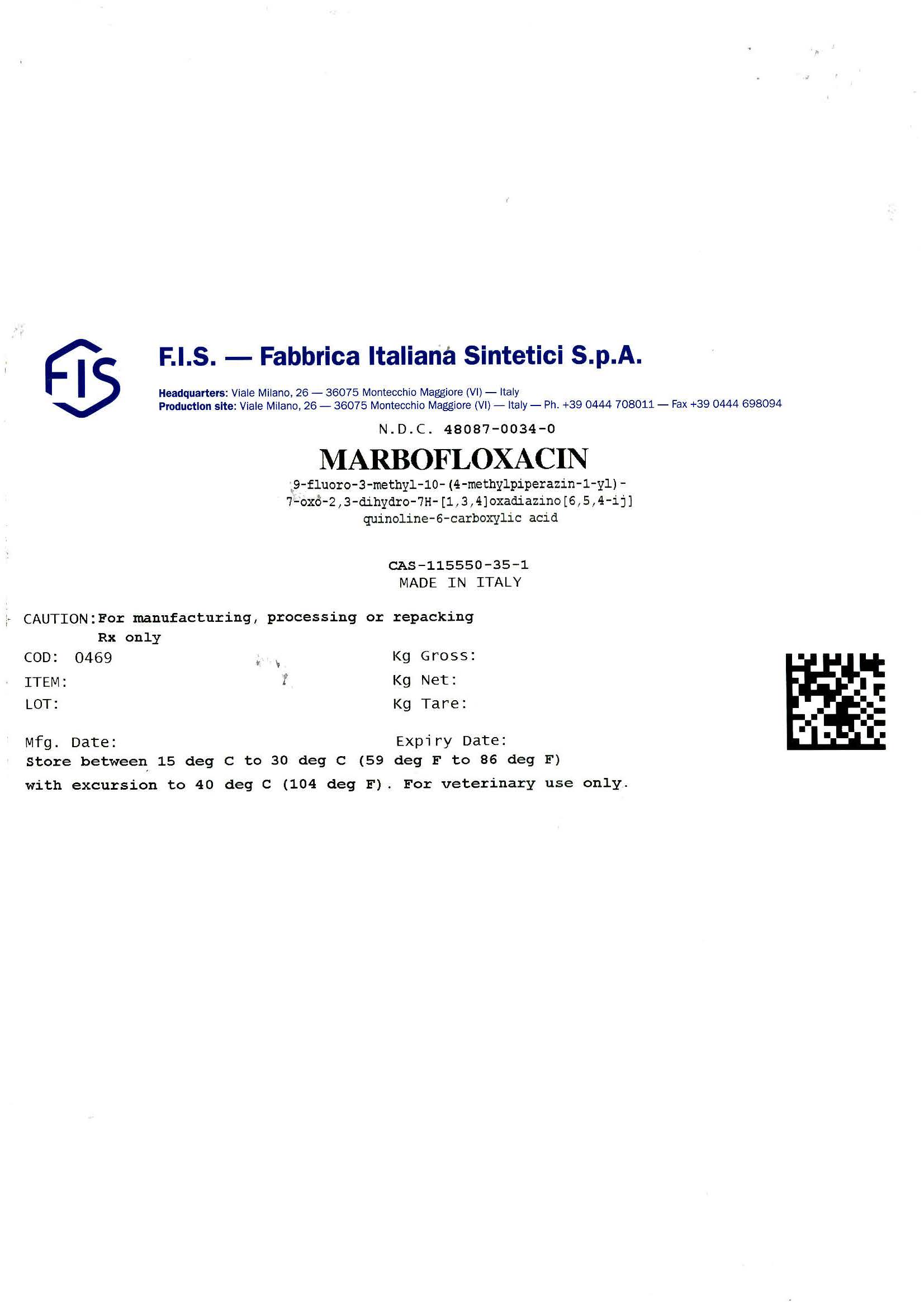 DRUG LABEL: MARBOFLOXACIN
NDC: 48087-0034 | Form: POWDER
Manufacturer: F.I.S. FABBRICA ITALIANA SINTETICI S.P.A.
Category: other | Type: BULK INGREDIENT - ANIMAL DRUG
Date: 20251015

ACTIVE INGREDIENTS: MARBOFLOXACIN 1 kg/1 kg

Marbofloxacin (0469) Manufacturer's Drum Label